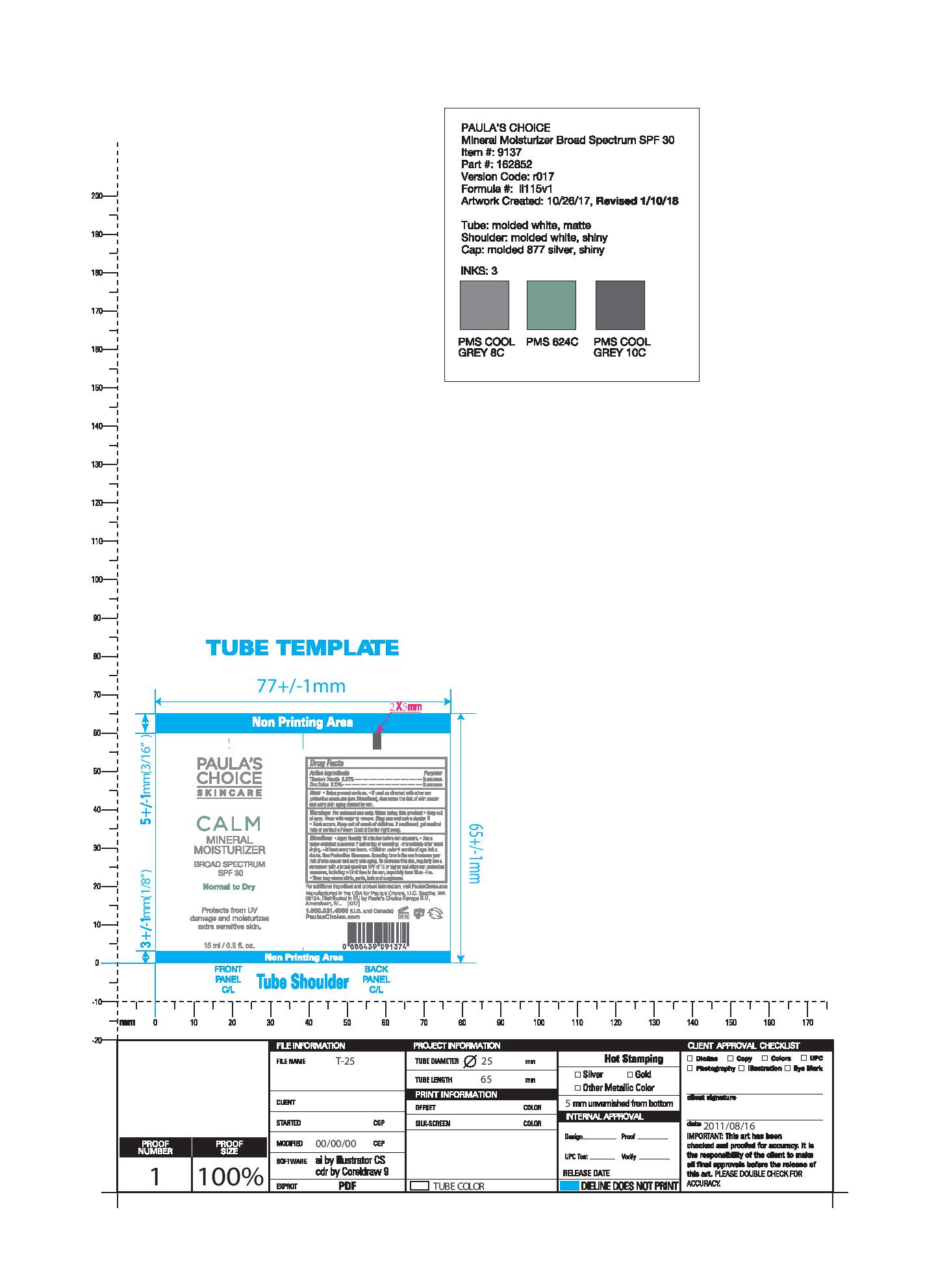 DRUG LABEL: Paulas Choice Calm Redness Relief SPF 30 Mineral Moisturizer (Normal to Dry)
NDC: 76144-913 | Form: LOTION
Manufacturer: Paula's Choice, LLC.
Category: otc | Type: HUMAN OTC DRUG LABEL
Date: 20220106

ACTIVE INGREDIENTS: TITANIUM DIOXIDE 38.5 mg/1 mL; ZINC OXIDE 31.2 mg/1 mL
INACTIVE INGREDIENTS: BUTYLENE GLYCOL; PENTYLENE GLYCOL; GLYCERIN; GLYCERYL MONOSTEARATE; PEG-100 STEARATE; CYCLOMETHICONE 5; SOY STEROL; OAT; .ALPHA.-TOCOPHEROL ACETATE, DL-; UBIDECARENONE; DIMETHICONE; EICOSYL POVIDONE; SUPEROXIDE DISMUTASE (SACCHAROMYCES CEREVISIAE); HYALURONATE SODIUM; ALLANTOIN; HYDROGENATED SOYBEAN LECITHIN; TETRAHEXYLDECYL ASCORBATE; WATER; ISONONYL ISONONANOATE; APRICOT KERNEL OIL; ALKYL (C12-15) BENZOATE

Paula's Choice Calm Redness Relief SPF 30 Mineral Moisturizer (Normal to Dry)

ACTIVE INGREDIENT

Titanium Dioxide 3.85%

Zinc Oxide 3.12%

PURPOSE

Sunscreen

Uses

Helps prevent sunburn. Decreases the risk of skin cancer and early skin agining caused by the sun if used as directed with other sun protection measures (see Directions).

Warnings

For external use only. Do not use on damaged or broken skin. When using this product, keep out of eyes. Rinse with water to remove. Stop use and ask a doctor if rash and irritation develops and lasts. Keep out of reach of children. If product is swallowed, get medical help or contact a Poison Control Center immediately.

Keep out of reach of children.

WHEN USING

Keep out of eyes. Rinse with water to remove.

Stop use and ask a doctor if rash and irritation develops and lasts.

Stop use if rash and irritation develop and lasts.

Other Information

Store at 20-25°C (68-77°F). You may report serious adverse reactions to 705 5th Avenue South, Suite 200, Seattle, WA 98104.

INACTIVE INGREDIENT

Water (Aqua), C12-15 Alkyl Benzoate, Isononl Isononanoate, Prunus Armeniaca (Apricot) Kernel Oil, Glyceryl Stearate, PEG-100 Stearate, Cyclopentasiloxane, Butylene Glycol, Pentylene Glycol, Cetearyl Alcohol, Dimethicone, VP/Eicosene Copolymer, Glycine Soja (Soybean) Sterols, Avena Sativa (Oat) Kernel Extract, Glycerin, Sodium Hyaluronate, Allantoin, Tocopheryl Acetate, Hydrogenated Lecithin, Tetrahexyldecyl Ascorbate, Superoxide Dismutase, Ubiquinone, Ceramide NG, Methicone, Palmitoyl Hexapeptide-12, PEG-10 Dimethicone, Cucumis Sativus (Cucumber) Fruit Extract, Caprylic/Capric Triglyceride, Tibehenin, Peg-10 Phytosterol, Sorbitan Stearate, Polyhydroxystearic Acid, Alumina, Polysorbate 20, Aluminum Stearate, Xanthan Gum, Caprylyl Glycol, Disodium EDTA, Ethylhexylglycerin, Phenoxyethanol, Chlorphenesin.